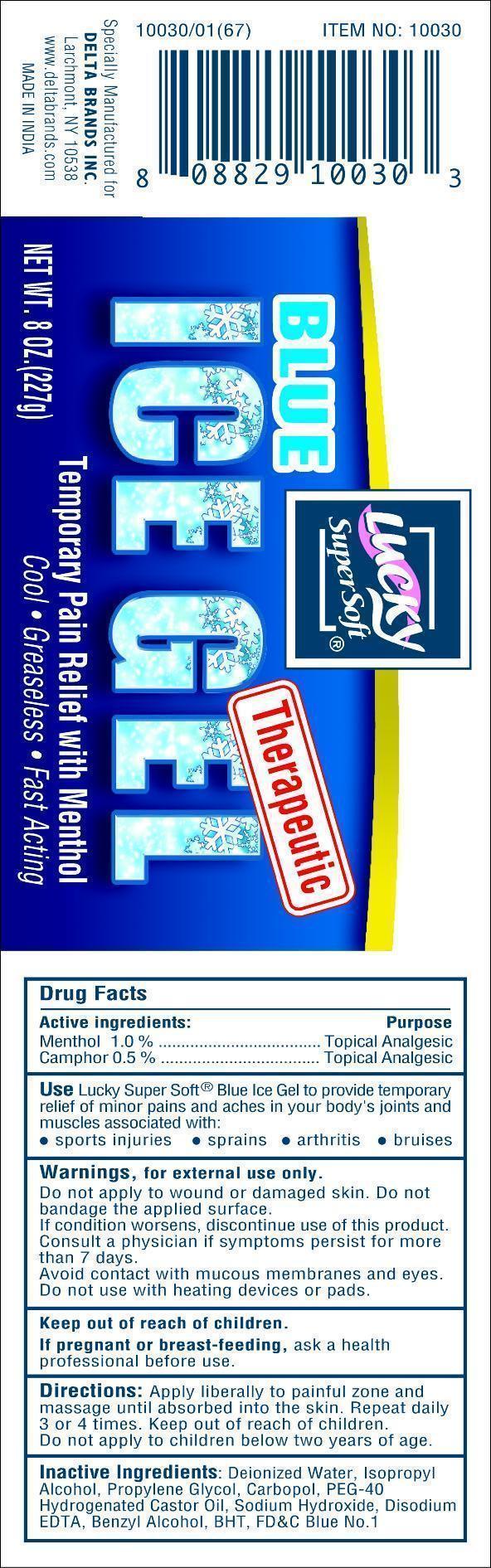 DRUG LABEL: Lucky Blue Ice
NDC: 47046-167 | Form: GEL
Manufacturer: Anicare Pharmaceuticals Pvt. Ltd.
Category: otc | Type: HUMAN OTC DRUG LABEL
Date: 20201220

ACTIVE INGREDIENTS: MENTHOL 1 g/100 g; CAMPHOR (SYNTHETIC) 0.5 g/100 g
INACTIVE INGREDIENTS: ALCOHOL; BENZYL ALCOHOL; BUTYLATED HYDROXYTOLUENE; CARBOMER 934; EDETATE DISODIUM; FD&C BLUE NO. 1; HYDROGENATED CASTOR OIL; ISOPROPYL ALCOHOL; POLYETHYLENE GLYCOL 200; SODIUM HYDROXIDE; WATER

Ice Gel

Active ingredients

Menthol 1.0%
Camphor 0.5%

Purpose

Topical Analgesic

Use

Lucky Super Soft Blue Ice Gel to provide temporary relief of minor pains and aches in your body's joints and muscles associated with:

- sports injuries
- sprains
- arthritis
- bruises

Warnings

for external use only
Do not apply to wound or damaged skin. Do not bandage the applied surface.
If condition worsens, discontinue use of this product.
Consult a physician if symptoms persist for more than 7 days.

Avoid contact with mucus membranes and eyes.

Do not use with heating devices or pads.

Keep out of reach of children

If pregnant or breast-feeding, ask a health professional before use

Directions

Apply liberally to painful zones and massage until absorbed into the skin. Repeat daily 3 or 4 times. Keep out of reach of children. Do not apply to children below two years of age.

Inactive Ingredients

Deionized Water, Isopropyl Alcohol, Propylene Glycol,Carbopol, PEG-40 Hydrogenated Castor Oil, Sodium Hydroxide,
Disodium EDTA, Benzyl Alcohol, BHT, FDC Blue No. 1